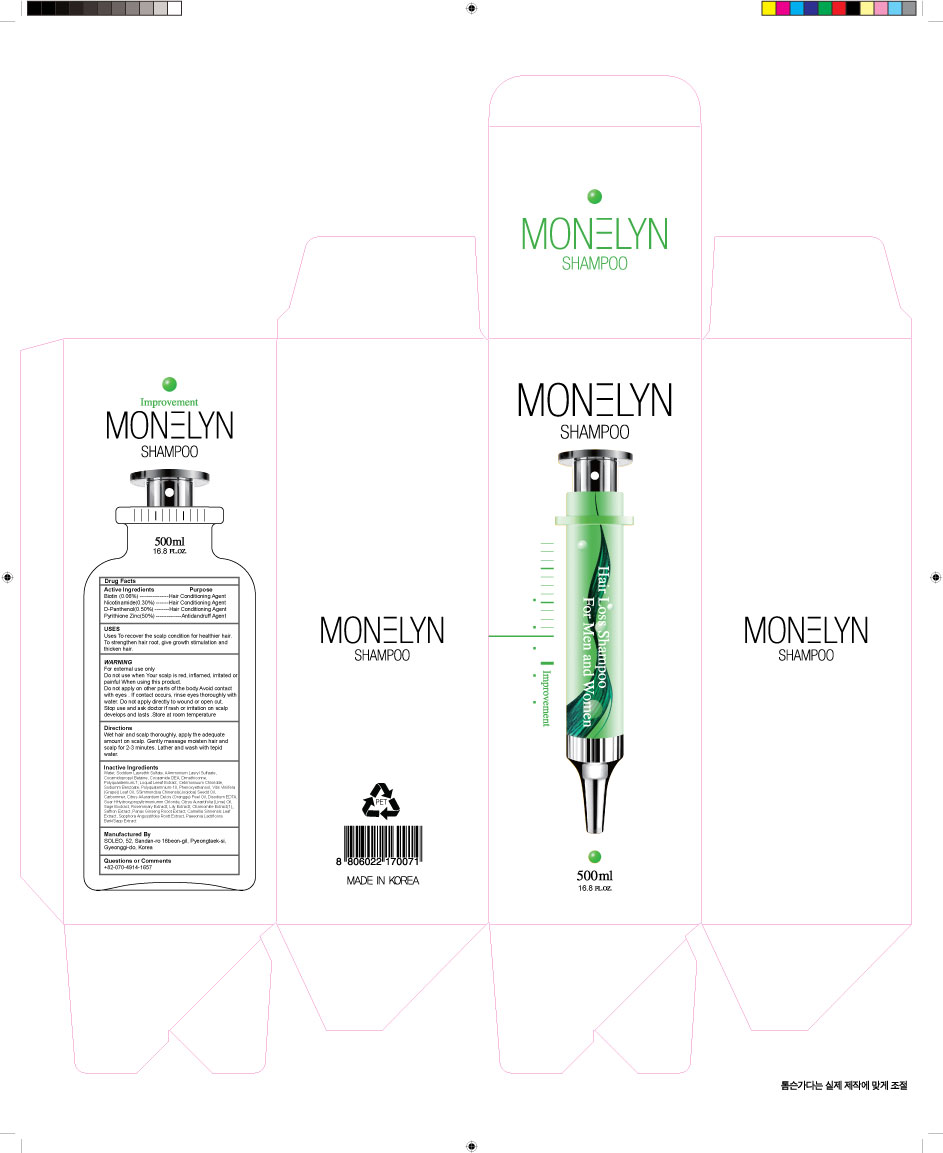 DRUG LABEL: DONG SUNG MONELYN
NDC: 70778-0002 | Form: SHAMPOO
Manufacturer: Daolcosmetic Co.,ltd
Category: otc | Type: HUMAN OTC DRUG LABEL
Date: 20160614

ACTIVE INGREDIENTS: PANTHENOL 0.5 g/100 mL; PYRITHIONE ZINC 2.1 g/100 mL; NIACINAMIDE 0.3 g/100 mL; BIOTIN 0.06 g/100 mL
INACTIVE INGREDIENTS: SODIUM LAURETH SULFATE; WATER

Drug Facts

ACTIVE INGREDIENT

Zinc Pyrithione Suspension (50%) 2.10%, Panthenol 0.50%, Niacinamide 0.30%, Biotin 0.06%

INACTIVE INGREDIENT

Sodium Polyoxyethylene Laurylether Sulfate, Ammonium Lauryl Sulfate Solution Cocamidopropylbetaine, Cocamide DEA, Dimethicone, Polyquaternium-7, Carbomers, Jojoba Oil, Disodium Edetate Hydrate, Guar Hydroxypropyltrimonium Chloride Sage Extract, Rosemary Extract, Lily Extract, Chamomile Extract, Saffron Extract,Ginseng Extract, Green Tea Extract, Sophora Extract, Paeonia Extract, Loquat Leaf Extract, Water

PURPOSE

Uses To recover the scalp condition for healthier hair. To strengthen hair root, give growth stimulation and thicken hair.

Keep out or reach of the children

INDICATIONS AND USAGE

Wet hair and scalp thoroughly, apply the adequate amount on scalp. Gently massage moisten hair and scalp for 2-3 minutes. Lather and wash with tepid water.

WARNINGS

For external use only
Do not use when Your scalp is red, inflamed, irritated or painful
When using this product
Do not apply on other parts of the body
Avoid contact with eyes . If contact occurs, rinse eyes thoroughly with water.
Do not apply directly to wound or open cut.
Stop use and ask doctor if rash or irritation on scalp develops and lasts .
Store at room temperature

DOSAGE AND ADMINISTRATION

For external use only